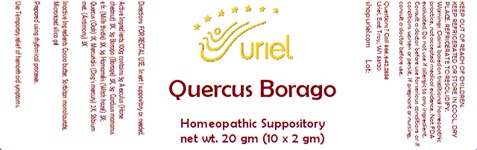 DRUG LABEL: Quercus Borago Adult Size
NDC: 48951-8115 | Form: SUPPOSITORY
Manufacturer: Uriel Pharmacy Inc.
Category: homeopathic | Type: HUMAN OTC DRUG LABEL
Date: 20241206

ACTIVE INGREDIENTS: AESCULUS HIPPOCASTANUM BARK 3 [hp_X]/1 g; BORAGE 3 [hp_X]/1 g; MILK THISTLE 3 [hp_X]/1 g; HAMAMELIS VIRGINIANA LEAF 3 [hp_X]/1 g; QUERCUS ROBUR WHOLE 1 [hp_X]/1 g; MERCURIALIS PERENNIS 2 [hp_X]/1 g; ANTIMONY 3 [hp_X]/1 g
INACTIVE INGREDIENTS: COCOA BUTTER; SORBITAN MONOLAURATE; SILICON DIOXIDE

Quercus Borago Adult Size

INDICATIONS AND USAGE

Directions: FOR RECTAL USE

DOSAGE AND ADMINISTRATION

Insert 1 suppository as needed.

ACTIVE INGREDIENT

Active Ingredients: 100g contains: 5g Aesculus (Horse chestnut) 3X, 5g Borago (Borage) 3X, 5g Carduus mar. (Milk thistle) 3X, 5g Hamamelis (Witch hazel) 3X; Quercus (Oak) 1X, Mercurialis per. (Dog’s mercury) 2X, Stibium met. (Antimony) 3X

INACTIVE INGREDIENT

Inactive Ingredients: Cocoa butter, Sorbitan monolaurate, Micronized silica gel

Prepared using rhythmical processes.

PURPOSE

Use: Temporary relief of hemorrhoid symptoms.

KEEP OUT OF REACH OF CHILDREN.

WARNINGS

KEEP REFRIGERATED OR STORE IN COOL, DRY PLACE. REFRIGERATE TO RESOLIDIFY.
Warnings: Claims based on traditional homeopathic practice, not accepted medical evidence. Not FDA evaluated. Do not use if allergic to any ingredient. Consult a doctor before use for serious conditions or if conditions worsen or persist. If pregnant or nursing, consult a doctor before use. Do not use if safety seals on box are broken or missing.

QUESTIONS

Questions? Call 866.642.2858 Uriel, East Troy, WI 53120 shopuriel.com Lot: